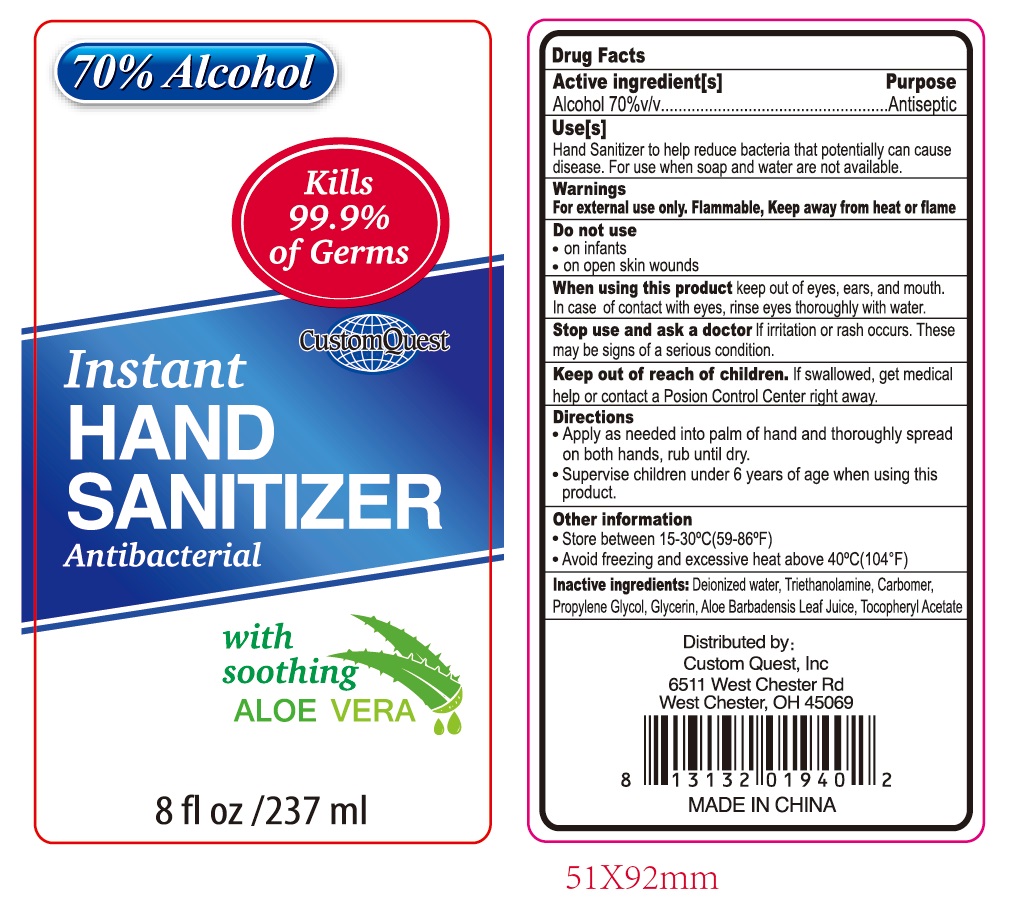 DRUG LABEL: CustomQuest instant Hand Sanitizer with soothing Aloe Vera
NDC: 52174-104 | Form: GEL
Manufacturer: Ningbo BST Clean And Care Products Co., Ltd
Category: otc | Type: HUMAN OTC DRUG LABEL
Date: 20200417

ACTIVE INGREDIENTS: alcohol 70 mL/100 mL
INACTIVE INGREDIENTS: WATER; PROPYLENE GLYCOL; ALOE VERA LEAF; CARBOMER 934; GLYCERIN; TROLAMINE; .ALPHA.-TOCOPHEROL ACETATE, D-

Drug facts

Active ingredient(s) Purpose

Alcohol 70% v/v ............... Antiseptic

PURPOSE

Hand sanitizer to help decrease bacteria on the skin.

KEEP OUT OF REACH OF CHILDREN

Children must be supervised in use of this product.

INDICATIONS AND USAGE

keep out of eyes

when water, soap and towel are not available

WARNINGS

For external use only.
Flammable. Keep away from fire or flame.

Stop using and ask medical attention if redness and irritation develop and persist for more than 72 hours.

Do not store above 40 Celsius Degree (105 Fahrenheit).

Do not use in mouth, ears or eyes. In case of contact, flush eyes with water.

DOSAGE AND ADMINISTRATION

Pump as needed into your palms and thoroughly spread on both hands, and rub the skin until dry.

Children must be supervised in use of this product.

INACTIVE INGREDIENT

Deionizer Water, Triethanolamine, Carbomer, Propylene Glycol, Glycerin, Aloe Barbadensis Leaf Juice, Tocopheryl Acetate